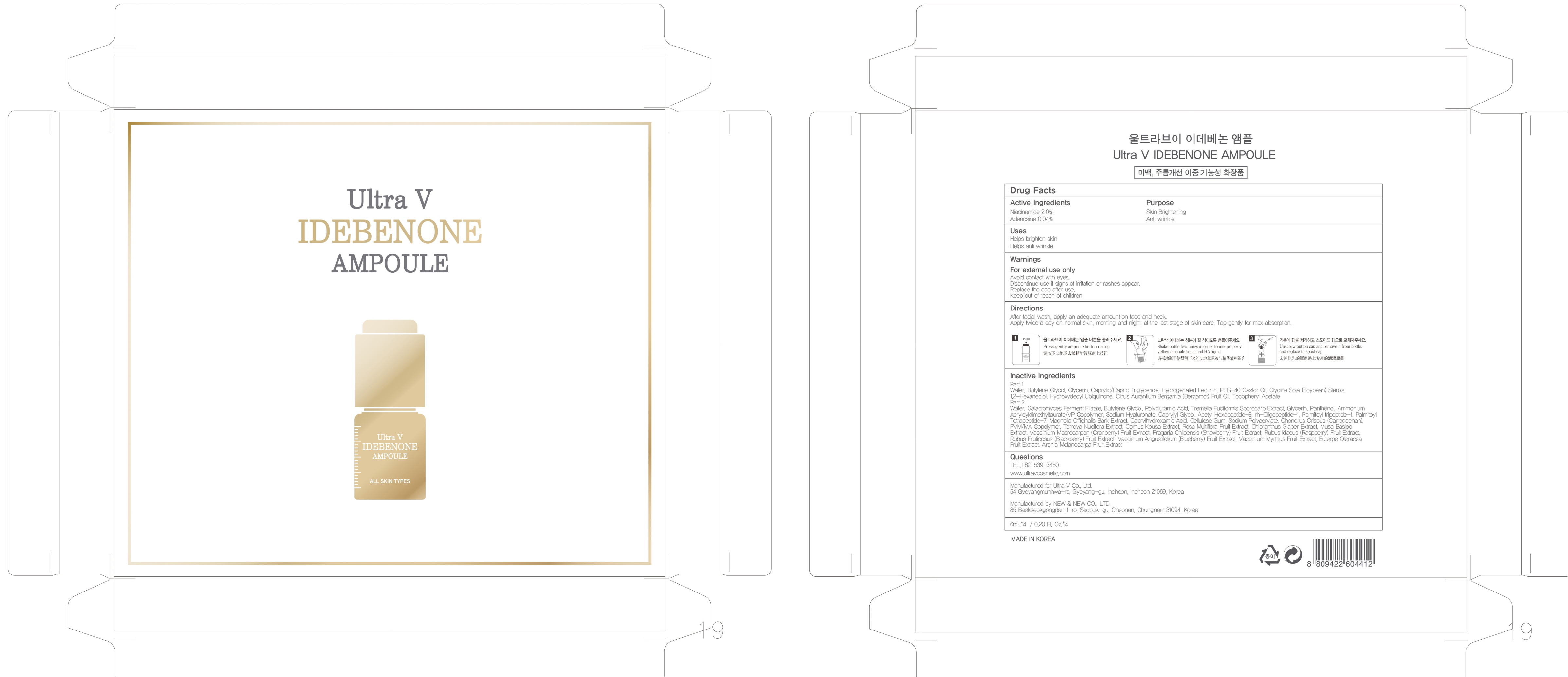 DRUG LABEL: Ultra V IDEBENONE AMPOULE
NDC: 71975-020 | Form: LIQUID
Manufacturer: Ultra V Co., Ltd
Category: otc | Type: HUMAN OTC DRUG LABEL
Date: 20200401

ACTIVE INGREDIENTS: Niacinamide 0.12 g/6 mL; Adenosine 0.002 g/6 mL
INACTIVE INGREDIENTS: Water; Butylene Glycol

ACTIVE INGREDIENT

Active ingredients: Niacinamide 2.0%, Adenosine 0.04%

INACTIVE INGREDIENT

Inactive ingredients:

Part 1: Water, Butylene Glycol , Glycerin , Caprylic/Capric Triglyceride , Hydrogenated Lecithin , PEG-40 Castor Oil , Glycine Soja (Soybean) Sterols , 1,2-Hexanediol , Hydroxydecyl Ubiquinone , Citrus Aurantium Bergamia (Bergamot) Fruit Oil, Tocopheryl Acetate

Part 2: Water, Galactomyces Ferment Filtrate , Butylene Glycol, Polyglutamic Acid, Tremella Fuciformis Sporocarp Extract , Glycerin, Panthenol, Ammonium Acryloyldimethyltaurate/VP Copolymer, Sodium Hyaluronate, Caprylyl Glycol, Acetyl Hexapeptide-8, rh-Oligopeptide-1, Palmitoyl tripeptide-1, Palmitoyl Tetrapeptide-7, Magnolia Officinalis Bark Extract, Caprylhydroxamic Acid, Cellulose Gum, Sodium Polyacrylate , Chondrus Crispus (Carrageenan) , PVM/MA Copolymer , Torreya Nucifera Extract , Cornus Kousa Extract , Rosa Multiflora Fruit Extract , Chloranthus Glaber Extract , Musa Basjoo Extract, Vaccinium Macrocarpon (Cranberry) Fruit Extract , Fragaria Chiloensis (Strawberry) Fruit Extract , Rubus Idaeus (Raspberry) Fruit Extract , Rubus Fruticosus (Blackberry) Fruit Extract , Vaccinium Angustifolium (Blueberry) Fruit Extract , Vaccinium Myrtillus Fruit Extract , Euterpe Oleracea Fruit Extract , Aronia Melanocarpa Fruit Extract

PURPOSE

Purpose: Skin Brightening, Anti wrinkle

WARNINGS

Warnings: For external use only. Avoid contact with eyes. Discontinue use if signs of irritation or rashes appear. Replace the cap after use. Keep out of reach of children.

KEEP OUT OF REACH OF CHILDREN

Uses

Helps brighten skin

Helps anti wrinkle

Directions

Directions: After facial wash, apply an adequate amount on face and neck. Apply twice a day on normal skin, morning and night, at the last stage of skin care. Tap gently for max absorption.

QUESTIONS

TEL,+82-539-3450

www.ultravcosmetic.com